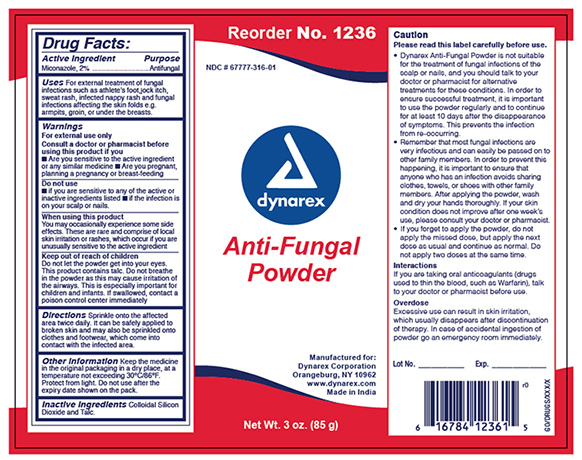 DRUG LABEL: Dynarex Antifungal Powder
NDC: 67777-316 | Form: POWDER
Manufacturer: Dynarex Corporation
Category: otc | Type: HUMAN OTC DRUG LABEL
Date: 20241120

ACTIVE INGREDIENTS: MICONAZOLE NITRATE 20 mg/1 g
INACTIVE INGREDIENTS: SILICON DIOXIDE; TALC

1236 Dynarex Antifungal Powder NDC 67777-316-01

Active Ingredient

Active Ingredient Purpose

Miconazol 2% Antifungal

Purpose

Uses

For external treatment of fungal infections such as athlete’s foot, jock itch, sweat rash, infected diaper rash and fungal infections affecting the skin folds e.g. armpits, groin, or under the breasts.

Warnings

For external use only.

Consult a doctor or pharmacist before using this product if you:

■ Are sensitive to the listed ingredients or any similar medications ■ Are pregnant, planning a pregnancy or breastfeeding

When using this product:

You may occasionally experience some side effects. These are rare and consist of local skin irritation or rashes, which occur if you are unusually sensitive to the ingredients listed.

Do Not Use

■ if you are sensitive to any of the active or inactive ingredients listed ■ if the infection is on your scalp or nails.

Cautions

Please read this label carefully before use.

• Dynarex Antifungal Powder is not suitable for the treatment of fungal infections of the scalp or nails, and you should talk to your doctor or pharmacist for alternative treatments for these conditions. In order to ensure successful treatment, it is important to use the powder regularly and to continue for at least 10 days after the disappearance of symptoms. This prevents the infection from reoccurring.

• Remember that most fungal infections are very infectious and can easily be passed on to other family members. In order to prevent this happening, it is important to ensure that anyone who has an infection avoids sharing clothes, towels, or shoes with other family members. After applying the powder, wash and dry your hands thoroughly. If your skin condition does not improve after one week’s use, please consult your doctor or pharmacist.

• If you forget to apply the powder, do not apply the missed dose, but apply the next dose as usual and continue as normal. Do not apply two doses at the same time.

Interactions

If you are taking oral anticoagulants (drugs used to thin the blood, such as Warfarin), talk to your doctor or pharmacist before use.

Overdose

Excessive use can result in skin irritation, which usually disappears after discontinuation of therapy. In case of accidental ingestion of powder go to the hospital immediately.

Directions

Sprinkle onto the affected area twice daily. It can be safely applied to broken skin and may also be sprinkled onto clothes and footwear, which come into contact with the infected area.

Other information

Keep the medicine in the original packaging in a dry place, at a temperature not exceeding 30ºC/86ºF. Protect from light. Do not use after the expiry date shown on the pack.

Keep Out Of Reach Of Children

Do not let the powder get into your eyes. This product contains talc. Do not breathe in the powder as this may cause irritation of the airways. This is especially important for children and infants. If swallowed, contact a poison control center immediately.

Inactive ingredients

Colloidal silicon dioxide, talc.

Principal Display panel

Dynarex Antifungal Powder 1236

AntiPowGP.jpg